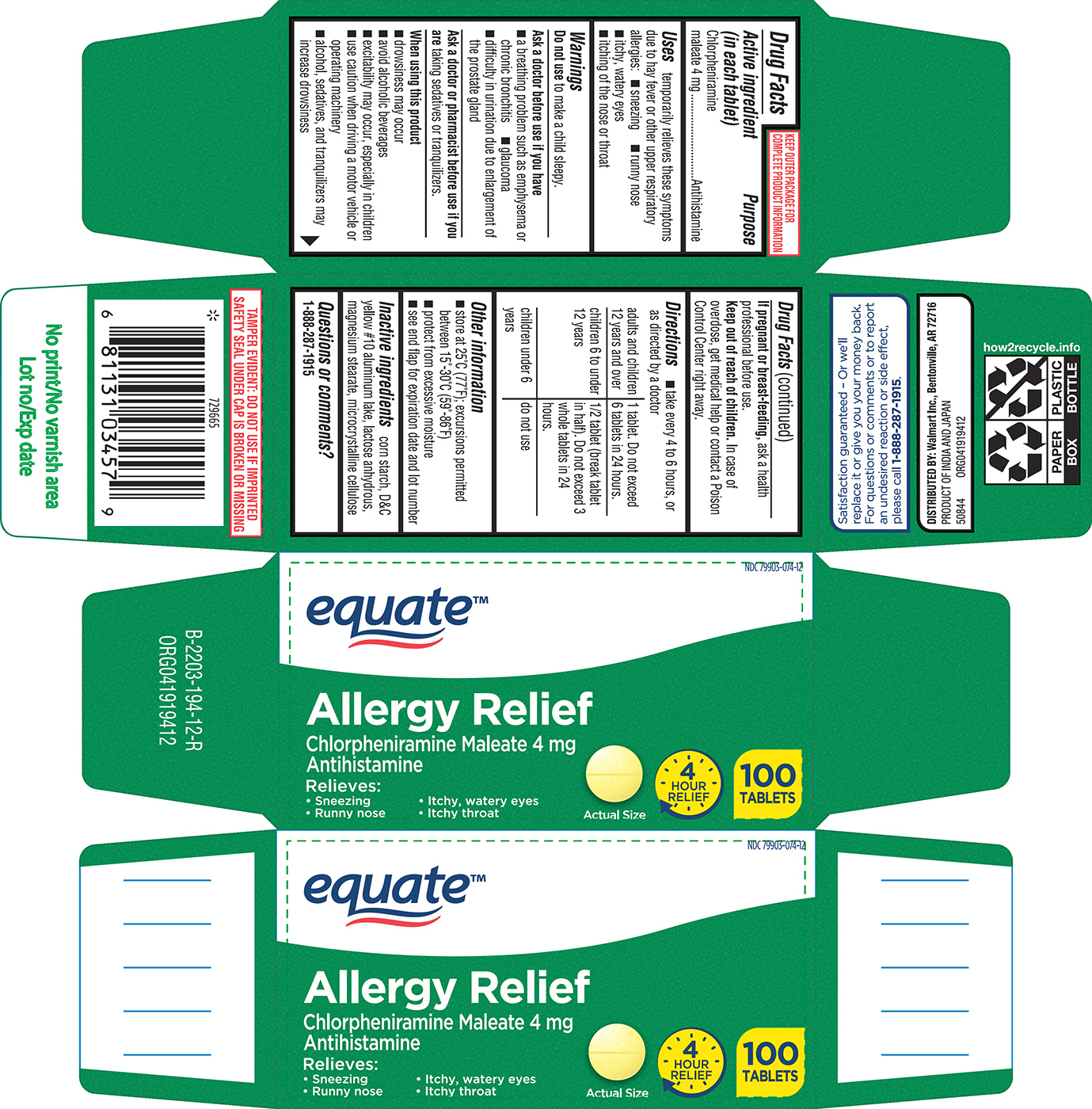 DRUG LABEL: Allergy Relief
NDC: 79903-074 | Form: TABLET
Manufacturer: WALMART INC.
Category: otc | Type: HUMAN OTC DRUG LABEL
Date: 20250904

ACTIVE INGREDIENTS: CHLORPHENIRAMINE MALEATE 4 mg/1 1
INACTIVE INGREDIENTS: STARCH, CORN; D&C YELLOW NO. 10 ALUMINUM LAKE; ANHYDROUS LACTOSE; MAGNESIUM STEARATE; MICROCRYSTALLINE CELLULOSE

Equate 44-194

Active ingredient (in each tablet)

Chlorpheniramine maleate 4 mg

Purpose

Antihistamine

Uses

temporarily relieves these symptoms due to hay fever or other upper respiratory allergies:

- sneezing
- runny nose
- itchy, watery eyes
- itching of the nose or throat

Warnings

Do not use

to make a child sleepy.

Ask a doctor before use if you have

- a breathing problem such as emphysema or chronic bronchitis
- glaucoma
- difficulty in urination due to enlargement of the prostate gland

Ask a doctor or pharmacist before use if you are

taking sedatives or tranquilizers.

When using this product

- drowsiness may occur
- avoid alcoholic beverages
- excitability may occur, especially in children
- use caution when driving a motor vehicle or operating machinery
- alcohol, sedatives, and tranquilizers may increase drowsiness

If pregnant or breast-feeding,

ask a health professional before use.

Keep out of reach of children.

In case of overdose, get medical help or contact a Poison Control Center right away.

Directions

- take every 4 to 6 hours, or as directed by a doctor

adults and children 12 years and over | 1 tablet. Do not exceed 6 tablets in 24 hours.
children 6 to under 12 years | 1/2 tablet (break tablet in half). Do not exceed 3 whole tablets in 24 hours.
children under 6 years | do not use

Other information

- store at 25°C (77°F); excursions permitted between 15°-30°C (59°-86°F)
- protect from excessive moisture
- see end flap for expiration date and lot number

Inactive ingredients

corn starch, D&C yellow #10 aluminum lake, lactose anhydrous, magnesium stearate, microcrystalline cellulose

Questions or comments?

1-888-287-1915

Principal display panel

equate™

NDC 79903-074-12

Allergy Relief
Chlorpheniramine Maleate 4 mg
Antihistamine

Relieves:
• Sneezing • Itchy, watery eyes
• Runny nose • Itchy throat

Actual Size

4
HOUR
RELIEF

100
TABLETS

TAMPER EVIDENT: DO NOT USE IF IMPRINTED
SAFETY SEAL UNDER CAP IS BROKEN OR MISSING

Satisfaction guaranteed – Or we’ll
replace it or give you your money back.
For questions or comments or to report
an undesired reaction or side effect,
please call 1-888-287-1915.

DISTRIBUTED BY: Walmart Inc., Bentonville, AR 72716
PRODUCT OF INDIA AND JAPAN
50844 ORG041919412

Equate 44-194